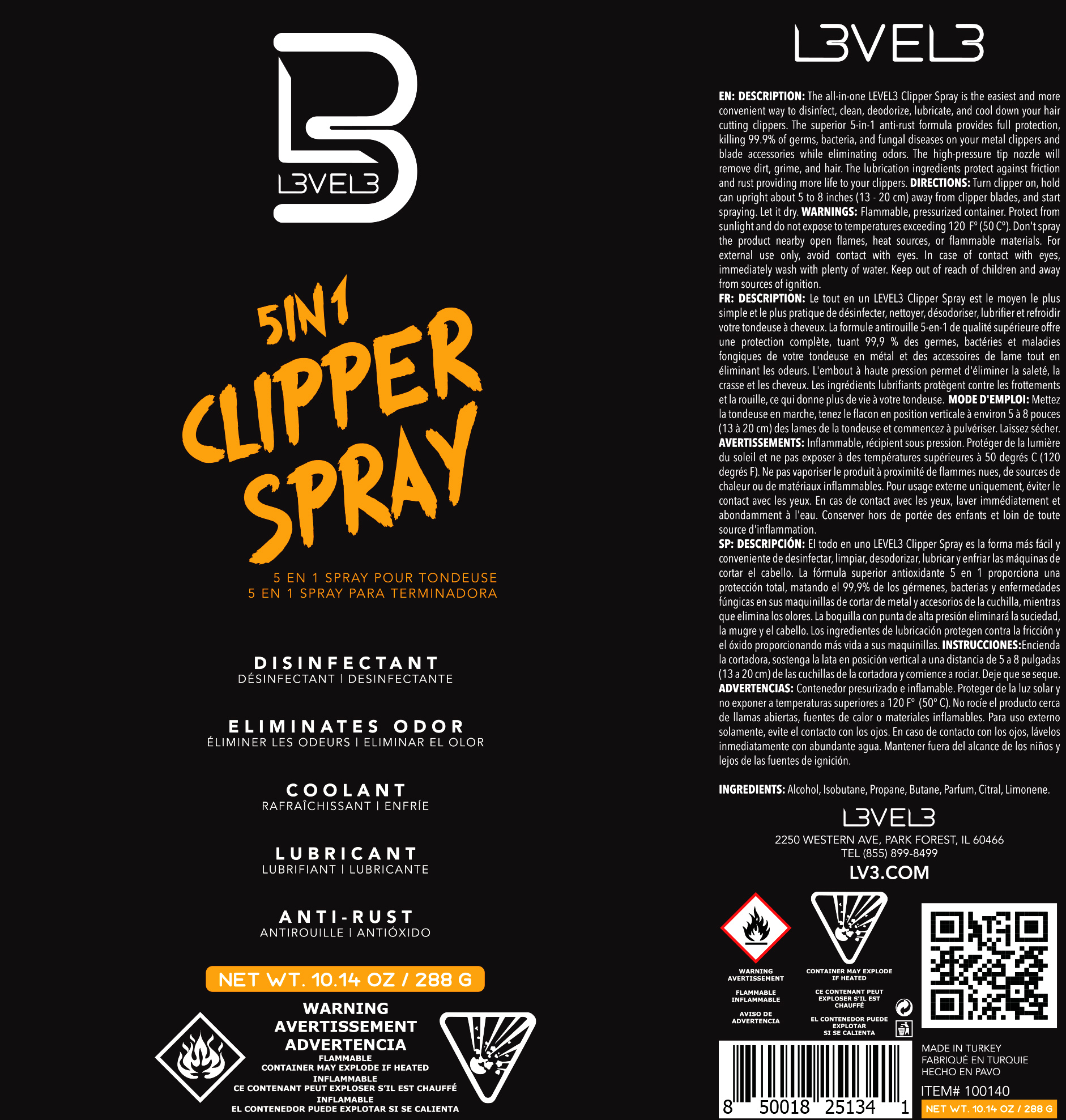 DRUG LABEL: 5 in 1 Clipper Spry
NDC: 80848-004 | Form: AEROSOL, SPRAY
Manufacturer: L3VEL3 LLC
Category: otc | Type: HUMAN OTC DRUG LABEL
Date: 20201016

ACTIVE INGREDIENTS: ALCOHOL 80.751 g/100 g
INACTIVE INGREDIENTS: CITRAL 0.015 g/100 g; LIMONENE, (+/-)- 0.08 g/100 g; PROPANE 3.346 g/100 g; BUTANE 13.379 g/100 g; ISOBUTANE 2.028 g/100 g

5in1 Clipper Spray

Purpose

Sanitizer

Description:

The all-in-one LEVEL3 Clipper Spray is the easiest and more convenient way to disinfect, clean, deodorize, lubricate, and cool down your hair cutting clippers. The superior 5-in-1 anti-rust formula provides full protection, killing 99.9% of germs, bacteria, and fungal diseases on your metal clippers and blade accessories while eliminating odors. The high-pressure tip nozzle will remove dirt, grime, and hair. The lubrication ingredients protect against friction and rust providing more life to your clippers.

Directions:

Turn clipper on, hold can upright about 5" to 8" away from clipper blades, and start spraying. Let it dry.

Warnings

Flammable. Pressurized container. Protect from sunlight and do not expose to temperatures exceeding 120 degrees Fahrenheit (50 degrees Celsius). Do not spray the product nearby open flames, heat sources, or flammable materials. For external use only, avoid contact with eyes. In case of contact with eyes, immediately wash with plenty of water. Keep out of reach of children and away from sources of ignition.

Keep out of reach of children.

Active Ingredient(s)

Alcohol

Inactive ingredients

Isobutane, Propane, Butane, Parfum, Citral, Limonene.

Package Label - Principal Display Panel

288 g NDC: 80848-004-01